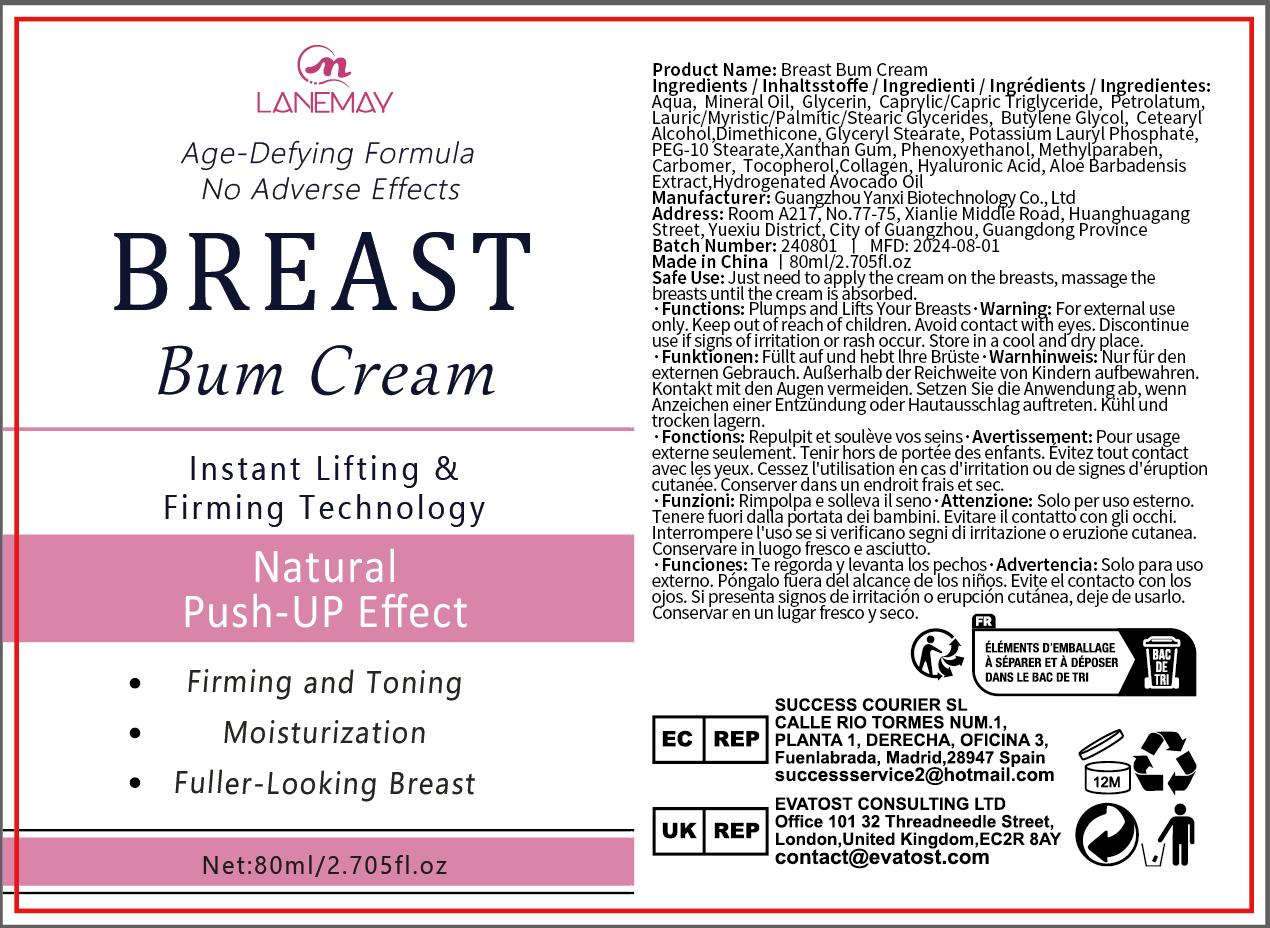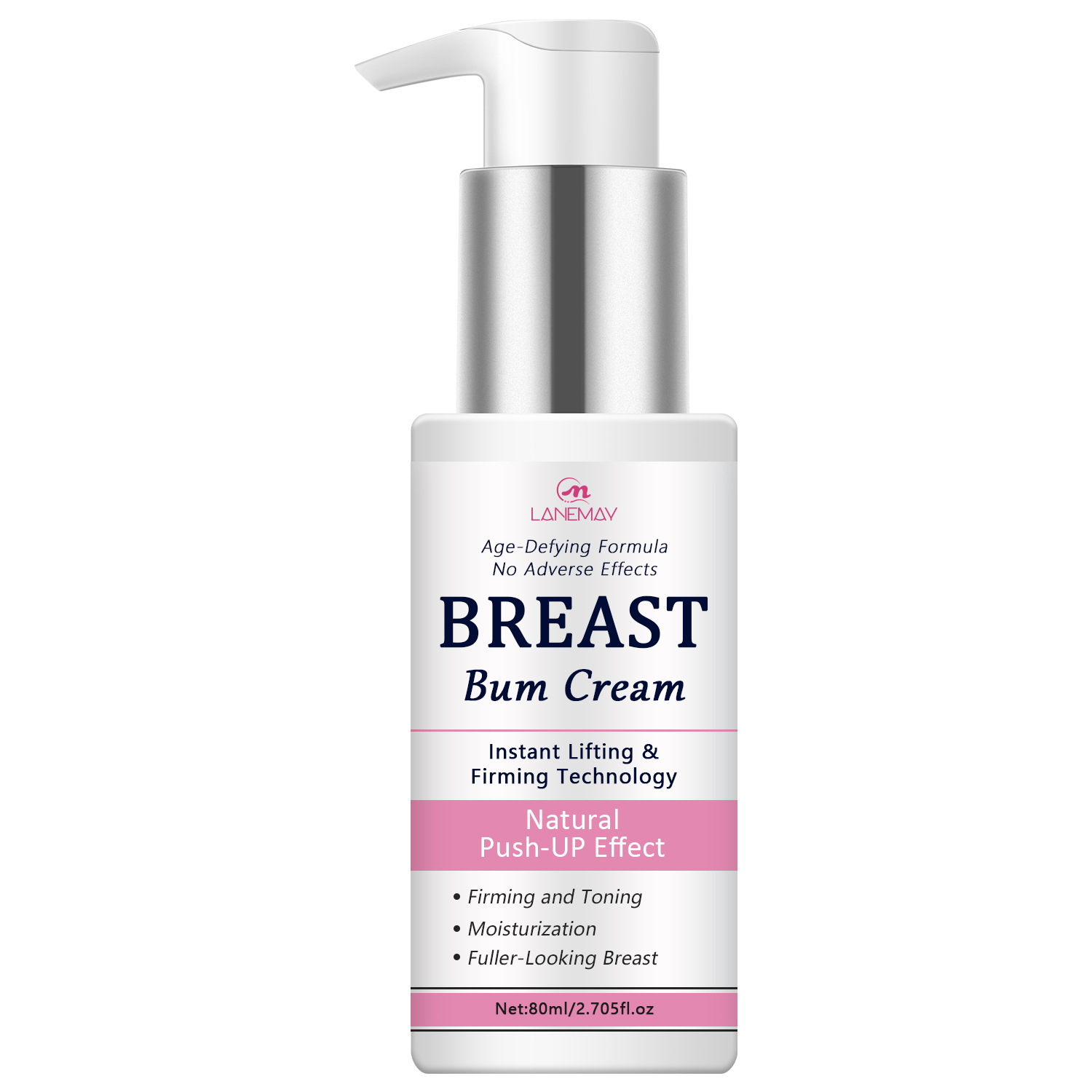 DRUG LABEL: Breast Bum Cream
NDC: 84025-197 | Form: CREAM
Manufacturer: Guangzhou Yanxi Biotechnology Co., Ltd
Category: otc | Type: HUMAN OTC DRUG LABEL
Date: 20240929

ACTIVE INGREDIENTS: GLYCERIN 3 mg/100 mL; MINERAL OIL 5 mg/100 mL
INACTIVE INGREDIENTS: WATER

DOSAGE AND ADMINISTRATION

Apply to the chest

WARNINGS

Keep out of children

INACTIVE INGREDIENT

Aqua

INDICATIONS AND USAGE

For chest care

Keep out of children

PURPOSE

Breast augmentation